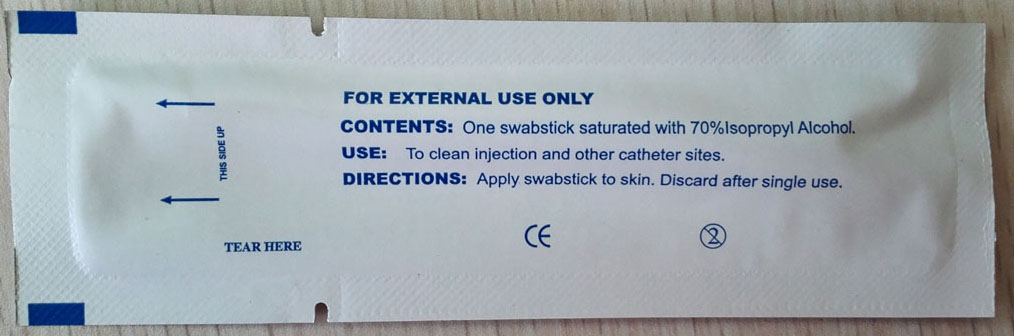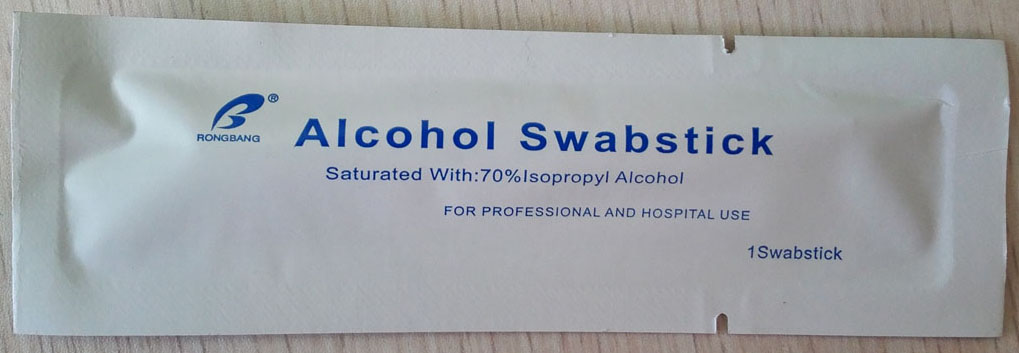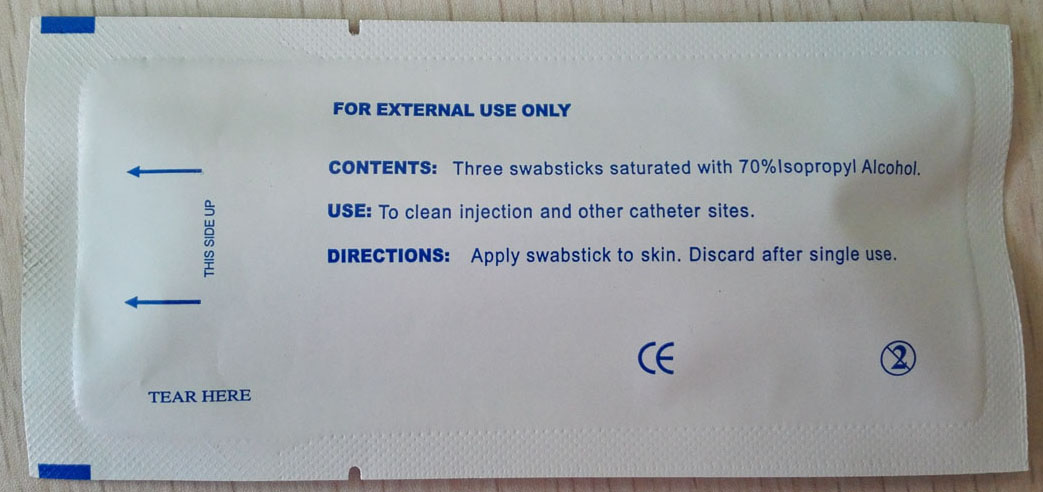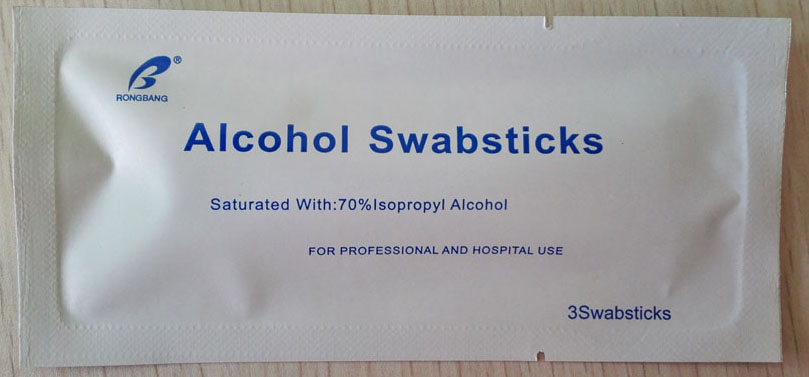 DRUG LABEL: Alcohol
NDC: 49953-2801 | Form: SWAB
Manufacturer: Dalian Rongbang Medical Healthy Devices Co., Ltd.
Category: otc | Type: HUMAN OTC DRUG LABEL
Date: 20161128

ACTIVE INGREDIENTS: ISOPROPYL ALCOHOL 7 mL/10 mL
INACTIVE INGREDIENTS: WATER

Alcohol Swabsticks

DOSAGE AND ADMINISTRATION

Two swabsticks saturated with 70% isopropyl alcohol.

Apply swabstick to skin.

INACTIVE INGREDIENT

water

INDICATIONS AND USAGE

To clean injection and other catheter sites.

Apply swabstick to skin.

KEEP OUT OF REACH OF CHILDREN

<Hospital professional use>

WARNINGS

For external use only

Discard after single use

PURPOSE

<To clean injection and other catheter sites.>

ACTIVE INGREDIENT

isopropyl alcohol 70 %

PACKAGE LABEL

<alcohol swabsticks saturated with 70% isopropyl alcohol, for professional and hosptial use>